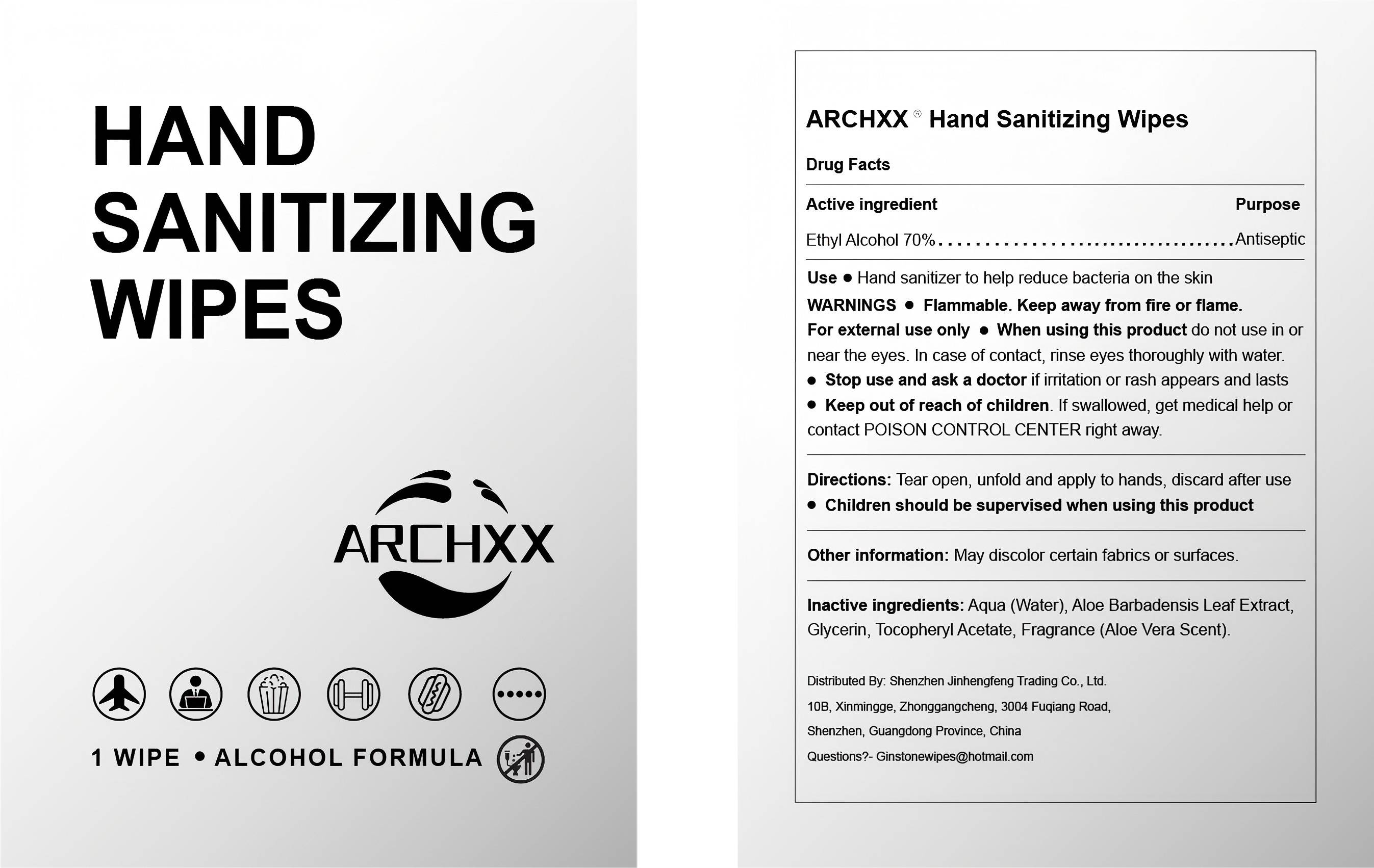 DRUG LABEL: Hand Sanitizing Wipes
NDC: 84449-007 | Form: PATCH
Manufacturer: SHENZHEN BENLIJU BIO-TECH CO.,LTD
Category: otc | Type: HUMAN OTC DRUG LABEL
Date: 20260105

ACTIVE INGREDIENTS: ALCOHOL 1.69 g/2.419 g
INACTIVE INGREDIENTS: GLYCERIN 0.002 g/2.419 g; TOCOPHERSOLAN 0.002 g/2.419 g; WATER 0.717 g/2.419 g; ALOE 0.008 g/2.419 g

ACTIVE INGREDIENT

Ethanol

PURPOSE

Hand sanitizer to help reduce bacteria on the skin

INDICATIONS AND USAGE

Hand sanitizer to help reduce bacteria on the skin

WARNINGS

Flammable,Keep away from fire or flame

When using this product do not use in ornear the eyes.In case of contact, rinse eyes thoroughly with water.

When using this product keep out of eyes.

Stop use and ask a doctor if irritation or rash appears and lasts.

Keep out of reach of children,lf swallowed, get medical help contact POISON CONTROL CENTER right away.

DOSAGE AND ADMINISTRATION

Directions: Tear open, unfold and apply to hands, discard after usee Children should be supervised when using this product.

STORAGE AND HANDLING

Store at room temperature.

INACTIVE INGREDIENT

Aqua (Water), Aloe Barbadensis Leaf Extract, Glycerin, Tocopheryl Acetate, Fragrance (Aloe Vera Scent).